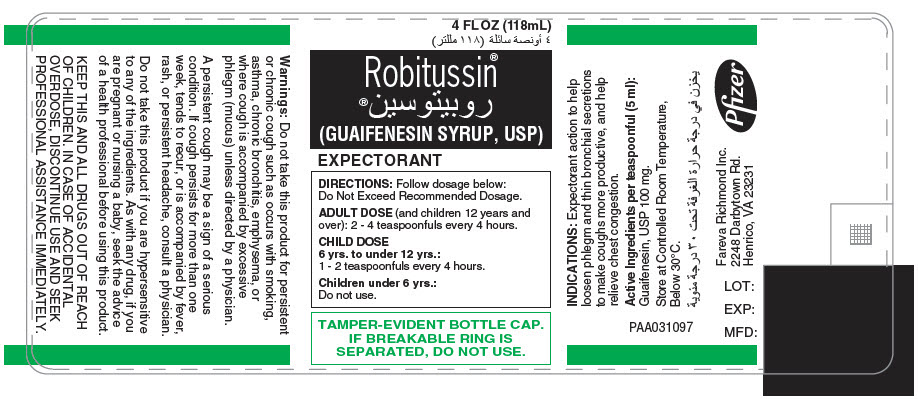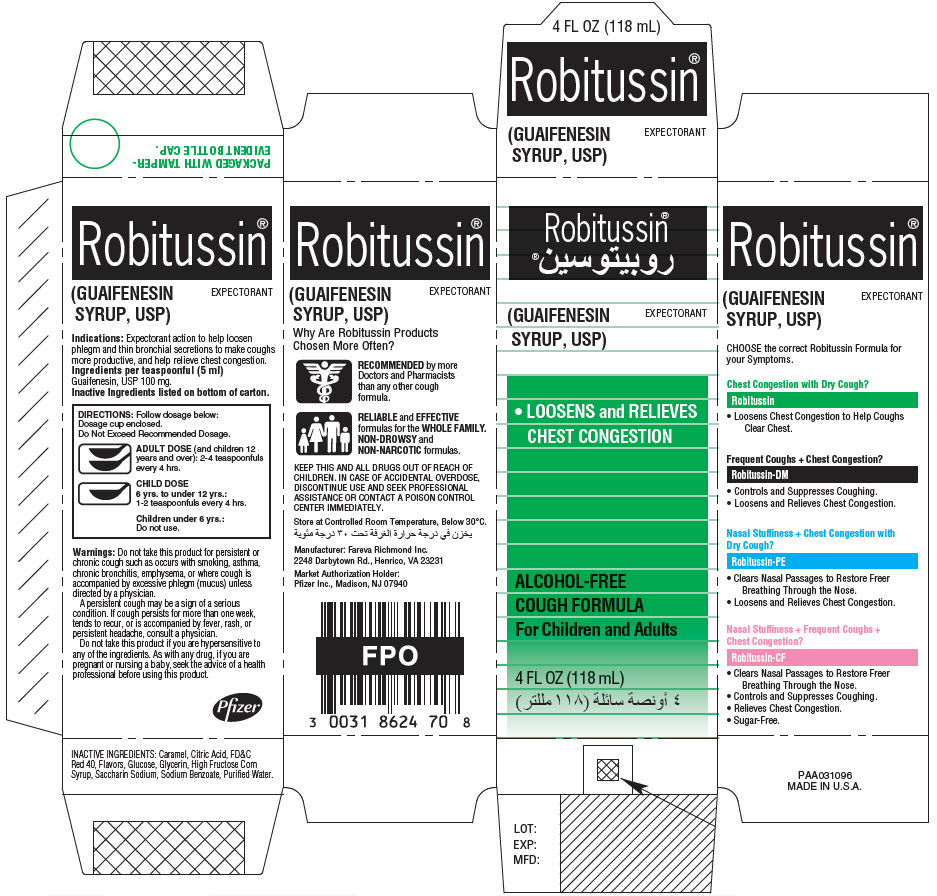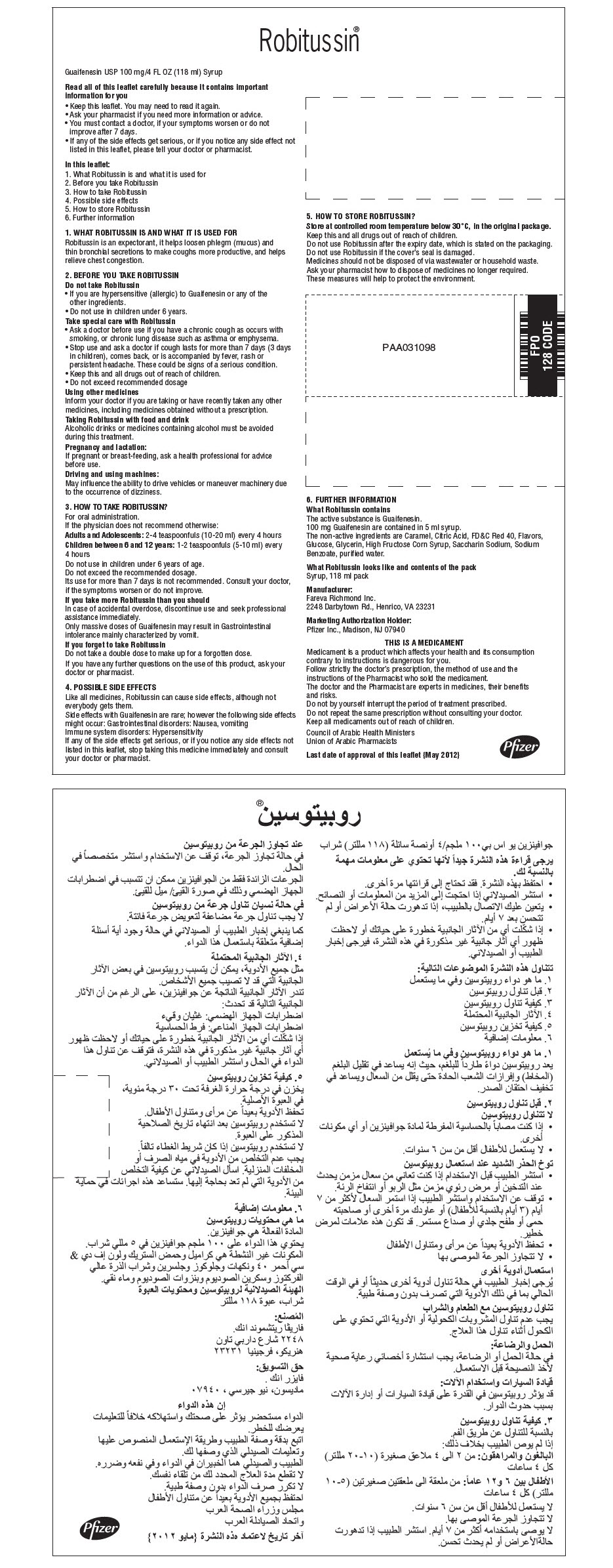 DRUG LABEL: ROBITUSSIN CHEST CONGESTION
NDC: 0031-8748 | Form: LIQUID
Manufacturer: Wyeth Consumer Healthcare LLC
Category: otc | Type: HUMAN OTC DRUG LABEL
Date: 20191204

ACTIVE INGREDIENTS: GUAIFENESIN 100 mg/5 mL
INACTIVE INGREDIENTS: ANHYDROUS CITRIC ACID; CARAMEL; FD&C RED NO. 40; GLYCERIN; HIGH FRUCTOSE CORN SYRUP; DEXTROSE, UNSPECIFIED FORM; MENTHOL, UNSPECIFIED FORM; PROPYLENE GLYCOL; SACCHARIN SODIUM; SODIUM BENZOATE; WATER

ROBITUSSIN® CHEST CONGESTION

PRINCIPAL DISPLAY PANEL - 118 mL Bottle Label

4 FL OZ (118mL)

Robitussin®

(GUAIFENESIN SYRUP, USP)

EXPECTORANT

DIRECTIONS: Follow dosage below:
Do Not Exceed Recommended Dosage.

ADULT DOSE (and children 12 years and
over): 2 - 4 teaspoonfuls every 4 hours.

CHILD DOSE
6 yrs. to under 12 yrs.:
1 - 2 teaspoonfuls every 4 hours.

Children under 6 yrs.:
Do not use.

TAMPER-EVIDENT BOTTLE CAP.
IF BREAKABLE RING IS
SEPARATED, DO NOT USE.

PRINCIPAL DISPLAY PANEL - 118 mL Bottle Carton

Robitussin®

(GUAIFENESIN
SYRUP, USP)

EXPECTORANT

- LOOSENS and RELIEVES
  CHEST CONGESTION

ALCOHOL-FREE
COUGH FORMULA
For Children and Adults

4 FL OZ (118 mL)